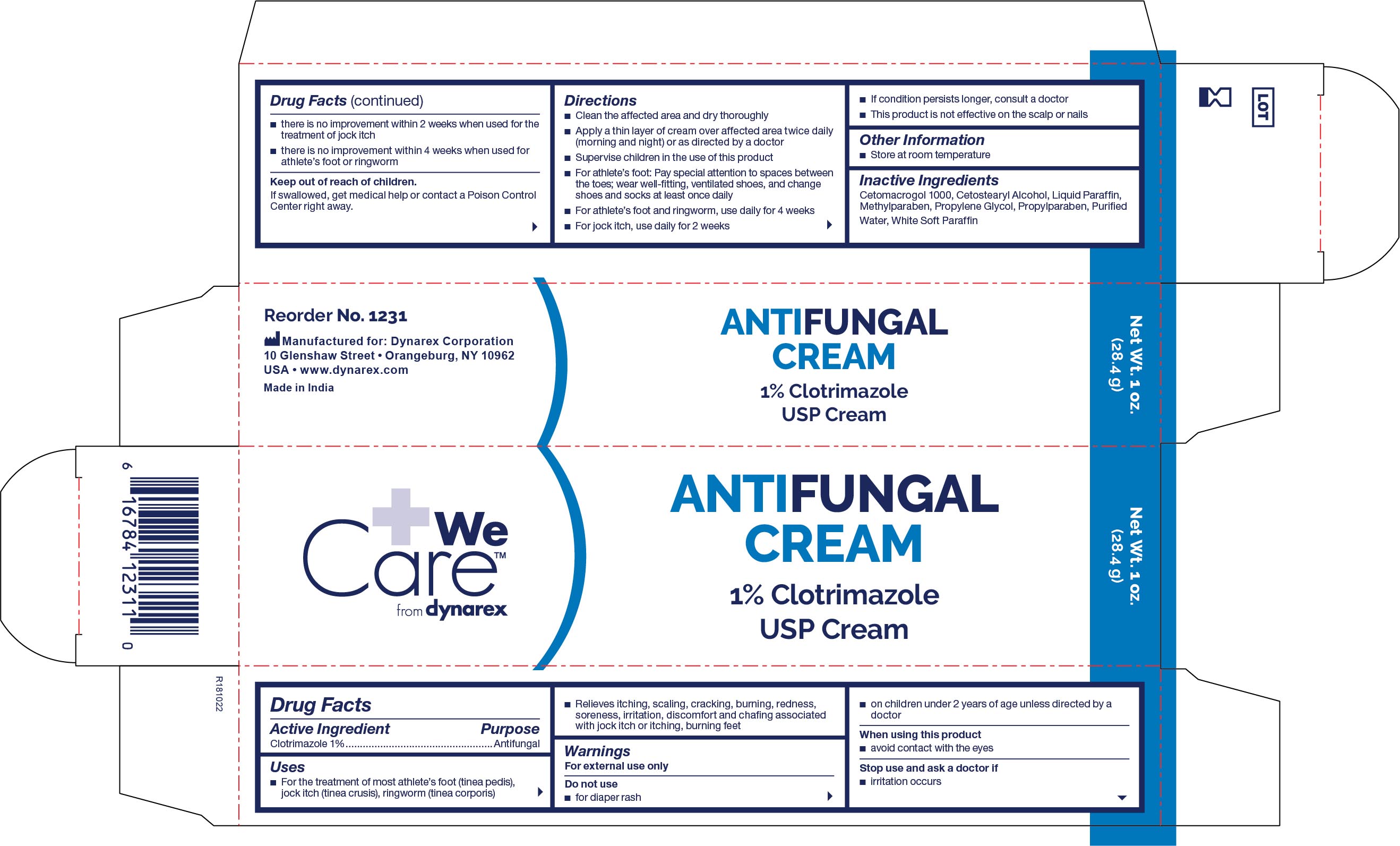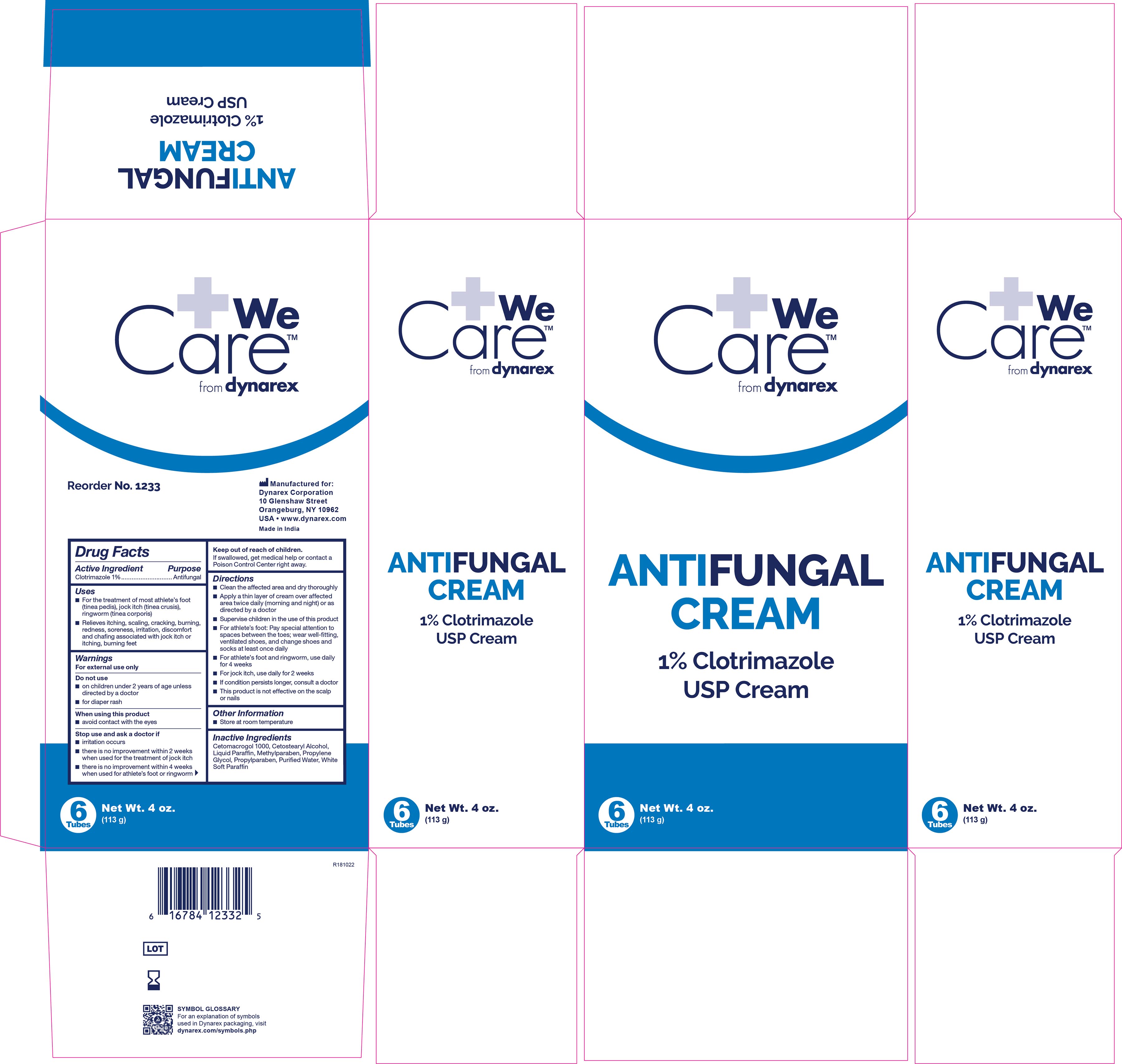 DRUG LABEL: Dynarex Antifungal
NDC: 67777-231 | Form: CREAM
Manufacturer: Dynarex Corporation
Category: otc | Type: HUMAN OTC DRUG LABEL
Date: 20241120

ACTIVE INGREDIENTS: CLOTRIMAZOLE 1 g/100 g
INACTIVE INGREDIENTS: PETROLATUM; CETETH-20; CETOSTEARYL ALCOHOL; LIGHT MINERAL OIL; METHYLPARABEN; PROPYLENE GLYCOL; PROPYLPARABEN; WATER

1231, 1233

Active Ingredient

Active Ingredient Purpose
Clotrimazole 1.0% Antifungal

Purpose

- For treatment of most athlete's foot (tinea pedis), jock itch (tinea crusis), Ringworm (tinea corporis).
- For the treatment of superficial skin infections caused by Yeast (Candida Albicans).
- Relieves itching, scaling, cracking, burning, redness, soreness, irritation discomfort and chafing associated with jock itch.

Warnings

Do not use:

- Do not use on children under 2 years of age unless directed by a doctor.
- Avoid contact with eyes.
- For athletes foot and ringworm - if irritation occurs, or if there is no improvement within 4 weeks, discontinue use and consult a doctor.
- For jock itch - if irritation occurs, or if there is no improvement within two weeks, discontinue use and consult a doctor.
- Keep out of reach of children. If swallowed, get medical help or contact a Poison Control Center right away.

Indications and Usage

- Clean the affected area and dry thoroughly. Apply a layer of cream over affected area twice daily (morning and night) or as directed by a doctor.
- Supervise children in the use of this product.
- For athlete's foot, pay special attention to spaces between toes: wear well fitting, ventilated shoes, and change shoes and socks at least once daily.

Dosage and Administration

- Foe athlete's foot and ringworm, use daily for 4 weeks.
- For jock itch, use daily for 2 weeks.If conditions persist longer, consult a doctor.
- This product is not effective on scalp or nails.

Keep Out Of Reach Of Children

INACTIVE INGREDIENTS

Inactive Ingredients: Cetomicrogol 1000, Cetostearyl alcohol, Liquid paraffin, Methylparaben, Propylene glycol, Propylparaben, Purified water, White soft paraben